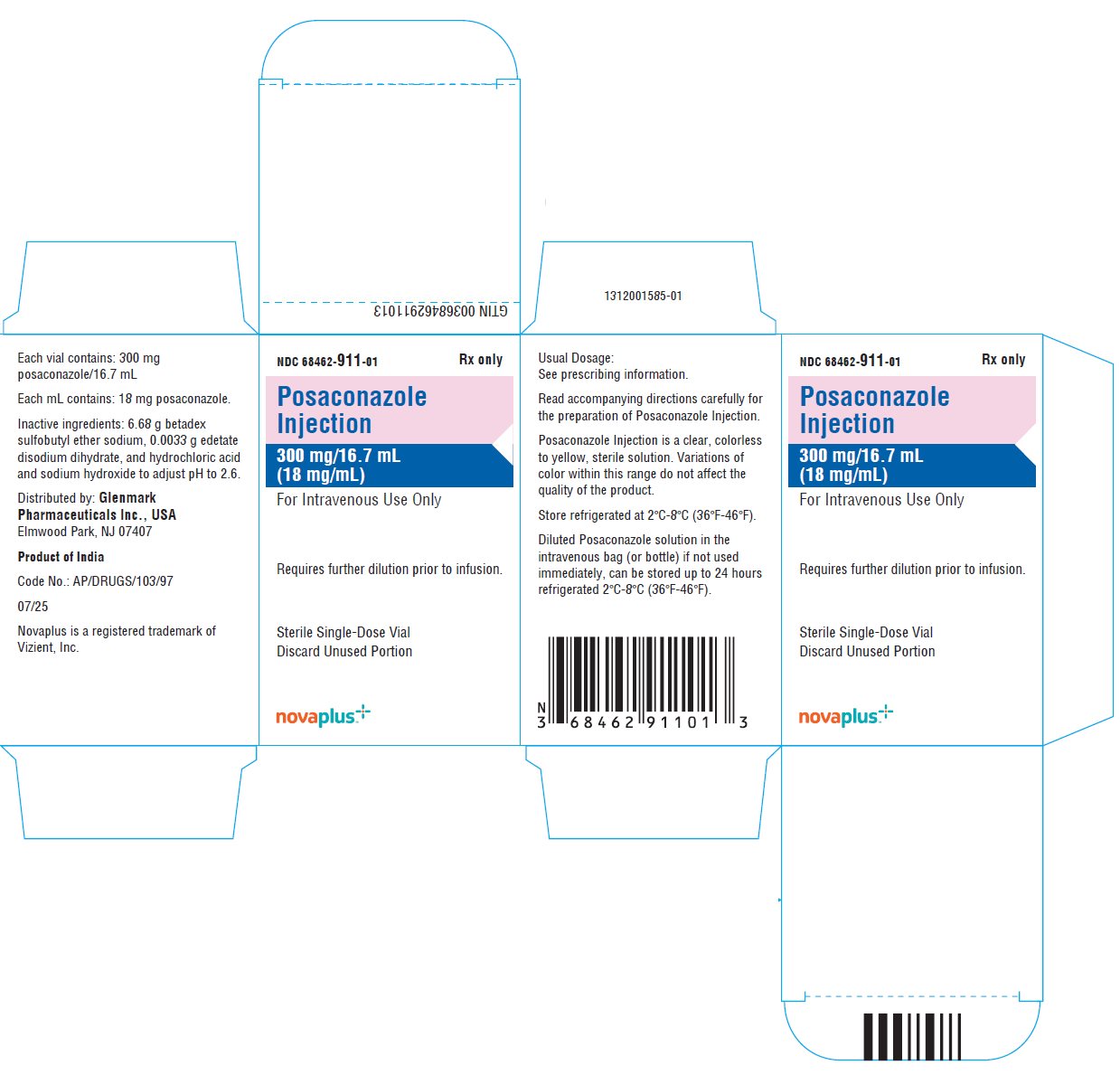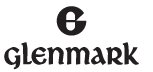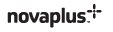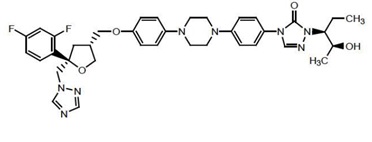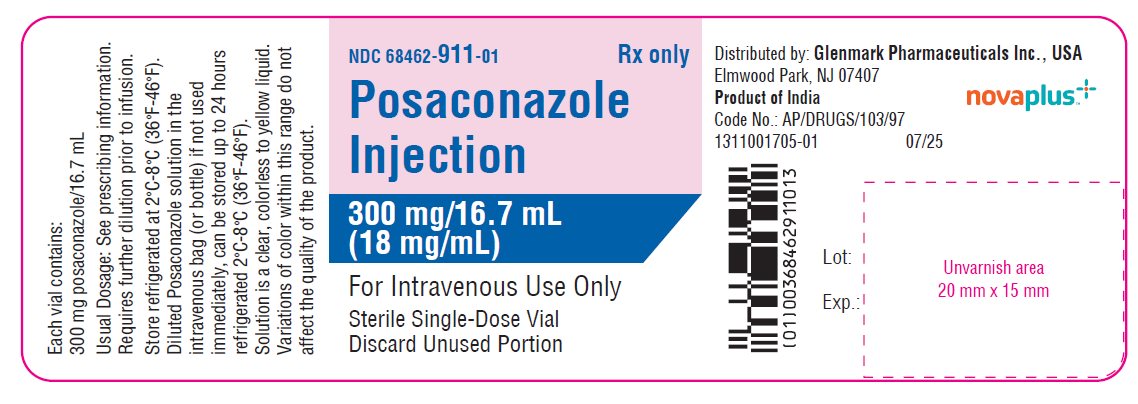 DRUG LABEL: posaconazole
NDC: 68462-911 | Form: INJECTION, SOLUTION
Manufacturer: GLENMARK PHARMACEUTICALS INC., USA
Category: prescription | Type: HUMAN PRESCRIPTION DRUG LABEL
Date: 20260211

ACTIVE INGREDIENTS: POSACONAZOLE 18 mg/1 mL
INACTIVE INGREDIENTS: BETADEX SULFOBUTYL ETHER SODIUM; EDETATE DISODIUM; HYDROCHLORIC ACID; SODIUM HYDROXIDE; WATER

HIGHLIGHTS OF PRESCRIBING INFORMATION

These highlights do not include all the information needed to use POSACONAZOLE INJECTION safely and effectively. See full prescribing information for POSACONAZOLE INJECTION.
POSACONAZOLE injection, for intravenous use
Initial U.S. Approval: 2006

RECENT MAJOR CHANGES

Warnings and Precautions, Pseudoaldosteronism (5.4) 10/2024

1 INDICATIONS AND USAGE

Posaconazole is an azole antifungal indicated as follows:

- Posaconazole injection is indicated for the treatment of invasive aspergillosis in adults and pediatric patients 13 years of age and older. (1.1)
- Posaconazole injection is indicated for the prophylaxis of invasive Aspergillus and Candida infections in patients who are at high risk of developing these infections due to being severely immunocompromised, such as hematopoietic stem cell transplant (HSCT) recipients with graft- versus-host disease (GVHD) or those with hematologic malignancies with prolonged neutropenia from chemotherapy as follows: (1.2)
  - Posaconazole injection: adults and pediatric patients 2 years of age and older.

2 DOSAGE AND ADMINISTRATION

- Posaconazole injection must be administered through an in-line filter.
- Administer posaconazole injection by intravenous infusion over approximately 90 minutes via a central venous line. (2.1)
- Do NOT administer posaconazole injection as an intravenous bolus injection. (2.1)

Table 1: Recommended Dosage in Adult Patients
Indication | Dosage Form, Dose, and Duration of Therapy
Treatment of invasive Aspergillosis | Posaconazole Injection: Loading dose: 300 mg posaconazole injection intravenously twice a day on the first day. Maintenance dose: 300 mg posaconazole injection intravenously once a day thereafter. Recommended total duration of therapy is 6 to 12 weeks. (2.2) Switching between the intravenous and Noxafil® delayed-release tablets is acceptable. A loading dose is not required when switching between formulations. (2.2)
Prophylaxis of invasive Aspergillus and Candida infections | Posaconazole Injection: Loading dose: 300 mg posaconazole injection intravenously twice a day on the first day. Maintenance dose: 300 mg posaconazole injection intravenously once a day thereafter. Duration of therapy is based on recovery from neutropenia or immunosuppression. (2.2, 2.3)

- For pediatric patients, see the Full Prescribing Information for dosing recommendations for posaconazole injection, based on the age and indication associated with the dosage form. (1.1, 1.2, 2.1, 2.3)

3 DOSAGE FORMS AND STRENGTHS

- Posaconazole injection: 300 mg per vial (18 mg per mL) in a single dose vial (3)

4 CONTRAINDICATIONS

- Known hypersensitivity to posaconazole or other azole antifungal agents. (4.1)
- Coadministration of posaconazole with the following drugs is contraindicated; posaconazole increases concentrations and toxicities of:
- Sirolimus (4.2, 5.1, 7.1)
- CYP3A4 substrates (pimozide, quinidine): can result in QTc interval prolongation and cases of torsades de pointes (TdP) (4.3,5.2, 7.2)
- HMG-CoA Reductase Inhibitors Primarily Metabolized through CYP3A4 (4.4,7.3)
- Ergot alkaloids (4.5, 7.4)
- Venetoclax: In patients with chronic lymphocytic leukemia (CLL) or small lymphocytic lymphoma (SLL) at initiation and during the ramp-up phase (4.6,5.11, 7.16)

5 WARNINGS AND PRECAUTIONS

- Calcineurin-Inhibitor Toxicity: Posaconazole increases concentrations of cyclosporine or tacrolimus; reduce dose of cyclosporine and tacrolimus and monitor concentrations frequently. (5.1)
- Arrhythmias and QTc Prolongation: Posaconazole has been shown to prolong the QTc interval and cause cases of TdP. Administer with caution to patients with potentially proarrhythmic conditions. Do not administer with drugs known to prolong QTc interval and metabolized through CYP3A4. (5.2)
- Electrolyte Disturbances: Monitor and correct, especially those involving potassium (K^+), magnesium (Mg^++), and calcium (Ca^++), before and during posaconazole therapy. (5.3)
- Pseudoaldosteronism: Manifested by the onset or worsening of hypertension, and abnormal laboratory findings. Monitor blood pressure and potassium levels, and manage as necessary. (5.4)
- Hepatic Toxicity: Elevations in liver tests may occur. Discontinuation should be considered in patients who develop abnormal liver tests or monitor liver tests during treatment. (5.5)
- Renal Impairment: Posaconazole injection should be avoided in patients with moderate or severe renal impairment (creatinine clearance <50 mL/min), unless an assessment of the benefit/risk to the patient justifies the use of posaconazole injection. (5.6, 8.6)
- Concomitant Use with Midazolam: Posaconazole can prolong hypnotic/sedative effects. Monitor patients and benzodiazepine receptor antagonists should be available. (5.7, 7.5)
- Vincristine Toxicity: Concomitant administration of azole antifungals, including posaconazole, with vincristine has been associated with neurotoxicity and other serious adverse reactions; reserve azole antifungals, including posaconazole, for patients receiving a vinca alkaloid, including vincristine, who have no alternative antifungal treatment options. (5.8, 7.10)
- Venetoclax Toxicity: Concomitant administration of posaconazole with venetoclax may increase venetoclax toxicities, including the risk of tumor lysis syndrome, neutropenia, and serious infections; monitor for toxicity and reduce venetoclax dose. (4.6, 5.11, 7.16)

6 ADVERSE REACTIONS

- Adult Patients: Common adverse reactions in studies with posaconazole in adults are diarrhea, nausea, fever, vomiting, headache, coughing, and hypokalemia. (6.1)
- Pediatric Patients: Common adverse reactions (incidence >20% receiving 6 mg/kg posaconazole injection) in a study in pediatric patients are pyrexia, febrile neutropenia, vomiting, mucosal inflammation, pruritus, hypertension, hypokalemia, and stomatitis. (6.1)

To report SUSPECTED ADVERSE REACTIONS, contact Glenmark Pharmaceuticals Inc., USA at 1 (888) 721-7115 or FDA at 1-800-FDA-1088 or www.fda.gov/medwatch.

7 DRUG INTERACTIONS

Interaction Drug | Interaction
Rifabutin, phenytoin, efavirenz | Avoid coadministration unless the benefit outweighs the risks (7.6, 7.7, 7.8)
Other drugs metabolized by CYP3A4 | Consider dosage adjustment and monitor for adverse effects and toxicity (7.1,7.10, 7.11)
Digoxin | Monitor digoxin plasma concentrations (7.12)
Fosamprenavir | Monitor for breakthrough fungal infections (7.6)

8 USE IN SPECIFIC POPULATIONS

- Pregnancy: Based on animal data, may cause fetal harm. (8.1)
- Pediatrics: Safety and effectiveness in patients younger than 2 years of age have not been established. (8.4)
- Severe Renal Impairment: Monitor closely for breakthrough fungal infections. (8.6)

FULL PRESCRIBING INFORMATION

1 INDICATIONS AND USAGE

1.1 Treatment of Invasive Aspergillosis

Posaconazole injection is indicated for the treatment of invasive aspergillosis in adults and pediatric patients 13 years of age and older.

1.2 Prophylaxis of Invasive Aspergillus and Candida Infections

Posaconazole injection is indicated for the prophylaxis of invasive Aspergillus and Candida infections in patients who are at high risk of developing these infections due to being severely immunocompromised, such as hematopoietic stem cell transplant (HSCT) recipients with graft-versus-host disease (GVHD) or those with hematologic malignancies with prolonged neutropenia from chemotherapy [see Clinical Studies (14.1)] as follows:

- Posaconazole injection: adults and pediatric patients 2 years of age and older

2 DOSAGE AND ADMINISTRATION

2.1 Important Administration Instructions

Posaconazole injection

- Administer via a central venous line, including a central venous catheter or peripherally inserted central catheter (PICC), by slow intravenous infusion over approximately 90 minutes [see Dosage and Administration (2.4)].
- If a central venous catheter is not available, posaconazole injection may be administered through a peripheral venous catheter by slow intravenous infusion over 30 minutes only as a single dose in advance of central venous line placement or to bridge the period during which a central venous line is replaced or is in use for other intravenous treatment.
- When multiple dosing is required, the infusion should be done via a central venous line.
- Do NOT administer posaconazole injection as an intravenous bolus injection

2.2 Dosing Regimen in Adult Patients

Table 1: Dosing Regimens in Adult Patients

Indication | Dose and Frequency | Duration of Therapy
Treatment of invasive Aspergillosis | Posaconazole Injection:; Loading dose:; 300 mg posaconazole injection intravenously twice a day on the first day.; Maintenance dose:; 300 mg posaconazole injection intravenously once a day, starting on the second day.; Switching between the intravenous and Noxafil® delayed-release tablets is acceptable. A loading dose is not required when switching between formulations. | Loading dose:; 1 day; Maintenance dose:; Recommended total duration of therapy is 6 to 12 weeks.
Prophylaxis of invasive Aspergillus and Candida infections | Posaconazole Injection: Loading dose: 300 mg posaconazole injection intravenously twice a day on the first day. Maintenance dose: 300 mg posaconazole injection intravenously once a day thereafter. | Loading dose: 1 day; Maintenance dose: Duration of therapy is based on recovery from neutropenia or immunosuppression.

2.3 Dosing Regimen in Pediatric Patients (ages 2 to less than 18 years of age)

The recommended dosing regimen of posaconazole injection for pediatric patients 2 to less than 18 years of age is shown in Table 2 [see Clinical Pharmacology (12.3)].

Table 2: Posaconazole Injection Dosing Regimens for Pediatric Patients (ages 2 to less than 18 years of age)

 |  | Recommended Pediatric Dosage and Formulation
Indication | Weight/Age | Injection | Duration of therapy
Prophylaxis of invasive Aspergillus and Candida infections | Less than or equal to 40 kg (2 to less than 18 years of age) Greater than 40 kg (2 to less than 18 years of age) | Loading dose: 6 mg/kg up to a maximum of 300 mg twice daily on the first day Maintenance dose: 6 mg/kg up to a maximum of 300 mg once daily | Duration of therapy is based on recovery from neutropenia or immunosuppression.
Treatment of invasive Aspergillosis | 13 to less than 18 years of age regardless of weight. | Loading dose: 300 mg posaconazole injection intravenously twice a day on the first day. Maintenance dose: 300 mg posaconazole injection intravenously once a day, starting on the second day. | Loading dose: 1 day Maintenance dose: Recommended total duration of therapy is 6 to 12 weeks.

2.4 Preparation, Intravenous Line Compatibility, and Administration of Posaconazole Injection

Preparation:

- Equilibrate the refrigerated vial of posaconazole injection to room temperature.
- To prepare the required dose, aseptically transfer one vial (16.7 mL) of posaconazole injection (containing 300 mg of posaconazole in solution) to an intravenous bag (or bottle) of a compatible admixture diluent (as described in Table 5), to achieve a final concentration of posaconazole that is between 1 mg/mL and 2 mg/mL. Use of other diluents is not recommended because they may result in particulate formation.
- Posaconazole injection is a single-dose sterile solution without preservatives. Discard any unused portion from the vial.
- Once admixed, the diluted solution of posaconazole in the intravenous bag (or bottle) should be used immediately. If not used immediately, the solution can be stored up to 24 hours refrigerated 2 to 8°C (36 to 46°F). Discard any unused portion.
- Parenteral drug products should be inspected visually for particulate matter prior to administration, whenever solution and container permit. Once admixed, the solution of posaconazole ranges from colorless to yellow. Variations of color within this range do not affect the quality of the product.
Intravenous Line Compatibility:
A study was conducted to evaluate physical compatibility of posaconazole injection with injectable drug products and commonly used intravenous diluents during simulated Y-site infusion. Compatibility was determined through visual observations, measurement of particulate matter and turbidity. Compatible diluents and drug products are listed in Tables 5 and 6 below. Any diluents or drug products not listed in the tables below should not be co-administered through the same intravenous line (or cannula).
- Posaconazole injection can be infused at the same time through the same intravenous line (or cannula) with the following compatible diluents:
Table 5: Compatible Diluents

0.45% sodium chloride

0.9% sodium chloride

5% dextrose in water

5% dextrose and 0.45% sodium chloride

5% dextrose and 0.9% sodium chloride

5% dextrose and 20 mEq potassium chloride

Amikacin sulfate

Caspofungin

Ciprofloxacin

Daptomycin

Dobutamine hydrochloride

Famotidine

Filgrastim

Gentamicin sulfate

Hydromorphone hydrochloride

Levofloxacin

Lorazepam

Meropenem

Micafungin

Morphine sulfate

Norepinephrine bitartrate

Potassium chloride

Vancomycin hydrochloride

Posaconazole injection must not be diluted with the following diluents:

Lactated Ringer’s solution

5% dextrose with Lactated Ringer’s solution

4.2% sodium bicarbonate

2.9 Dosage Adjustments in Patients with Renal Impairment

- Posaconazole injection should be avoided in patients with moderate or severe renal impairment (eGFR <50 mL/min), unless an assessment of the benefit/risk to the patient justifies the use of posaconazole injection.
- In patients with moderate or severe renal impairment (estimated glomerular filtration rate (eGFR) <50 mL/min), receiving the posaconazole injection, accumulation of the intravenous vehicle, Betadex Sulfobutyl Ether Sodium (SBECD), is expected to occur. Serum creatinine levels should be closely monitored in these patients, and, if increases occur, consideration should be given to changing to oral posaconazole therapy.

3 DOSAGE FORMS AND STRENGTHS

Posaconazole injection
Posaconazole injection (300 mg per vial) is available as a clear, colorless to yellow sterile liquid in a single-dose vial.

4 CONTRAINDICATIONS

4.1 Hypersensitivity

Posaconazole is contraindicated in persons with known hypersensitivity to posaconazole or other azole antifungal agents.

4.2 Use with Sirolimus

Posaconazole is contraindicated with sirolimus. Concomitant administration of posaconazole with sirolimus increases the sirolimus blood concentrations by approximately 9-fold and can result in sirolimus toxicity [see Drug Interactions (7.1) and Clinical Pharmacology (12.3)].

4.3 QT Prolongation with Concomitant Use with CYP3A4 Substrates

Posaconazole is contraindicated with CYP3A4 substrates that prolong the QT interval. Concomitant administration of posaconazole with the CYP3A4 substrates, pimozide and quinidine may result in increased plasma concentrations of these drugs, leading to QTc prolongation and cases of torsades de pointes [see Warnings and Precautions (5.2) and Drug Interactions (7.2)].

4.4 HMG-CoA Reductase Inhibitors Primarily Metabolized Through CYP3A4

Coadministration with the HMG-CoA reductase inhibitors that are primarily metabolized through CYP3A4 (e.g., atorvastatin, lovastatin, and simvastatin) is contraindicated since increased plasma concentration of these drugs can lead to rhabdomyolysis [see Drug Interactions (7.3) and Clinical Pharmacology (12.3)].

4.5 Use with Ergot Alkaloids

Posaconazole may increase the plasma concentrations of ergot alkaloids (ergotamine and dihydroergotamine) which may lead to ergotism [see Drug Interactions (7.4)].

4.6 Use with Venetoclax

Coadministration of posaconazole with venetoclax at initiation and during the ramp-up phase is contraindicated in patients with chronic lymphocytic leukemia (CLL) or small lymphocytic lymphoma (SLL) due to the potential for increased risk of tumor lysis syndrome [see Warnings and Precautions (5.11) and Drug Interactions (7.16)].

5 WARNINGS AND PRECAUTIONS

5.1 Calcineurin-Inhibitor Toxicity

Concomitant administration of posaconazole with cyclosporine or tacrolimus increases the whole blood trough concentrations of these calcineurin-inhibitors [see Drug Interactions (7.1) and Clinical Pharmacology (12.3)]. Nephrotoxicity and leukoencephalopathy (including deaths) have been reported in clinical efficacy studies in patients with elevated cyclosporine or tacrolimus concentrations. Frequent monitoring of tacrolimus or cyclosporine whole blood trough concentrations should be performed during and at discontinuation of posaconazole treatment and the tacrolimus or cyclosporine dose adjusted accordingly.

5.2 Arrhythmias and QT Prolongation

Some azoles, including posaconazole, have been associated with prolongation of the QT interval on the electrocardiogram. In addition, cases of torsades de pointes have been reported in patients taking posaconazole.

Results from a multiple time-matched ECG analysis in healthy volunteers did not show any increase in the mean of the QTc interval. Multiple, time-matched ECGs collected over a 12-hour period were recorded at baseline and steady-state from 173 healthy male and female volunteers (18-85 years of age) administered Noxafil® (posaconazole) oral suspension 400 mg twice daily with a high-fat meal. In this pooled analysis, the mean QTc (Fridericia) interval change from baseline was –5 msec following administration of the recommended clinical dose. A decrease in the QTc(F) interval (–3 msec) was also observed in a small number of subjects (n=16) administered placebo. The placebo-adjusted mean maximum QTc(F) interval change from baseline was <0 msec (–8 msec). No healthy subject administered posaconazole had a QTc(F) interval ≥500 msec or an increase ≥60 msec in their QTc(F) interval from baseline.

Posaconazole should be administered with caution to patients with potentially proarrhythmic conditions. Do not administer with drugs that are known to prolong the QTc interval and are metabolized through CYP3A4 [see Contraindications (4.3) and Drug Interactions (7.2)].

5.3 Electrolyte Disturbances

Electrolyte disturbances, especially those involving potassium, magnesium or calcium levels, should be monitored and corrected as necessary before and during posaconazole therapy.

5.4 Pseudoaldosteronism

Pseudoaldosteronism, manifested by the onset of hypertension or worsening of hypertension, and abnormal laboratory findings (hypokalemia, low serum renin and aldosterone, and elevated 11-deoxycortisol), has been reported with posaconazole use in the postmarket setting. Monitor blood pressure and potassium levels and manage as necessary. Management of pseudoaldosteronism may include discontinuation of Noxafil, substitution with an appropriate antifungal drug that is not associated with pseudoaldosteronism, or use of aldosterone receptor antagonists.

5.5 Hepatic Toxicity

Hepatic reactions (e.g., mild to moderate elevations in alanine aminotransferase (ALT), aspartate aminotransferase (AST), alkaline phosphatase, total bilirubin, and/or clinical hepatitis) have been reported in clinical trials. The elevations in liver tests were generally reversible on discontinuation of therapy, and in some instances these tests normalized without drug interruption. Cases of more severe hepatic reactions including cholestasis or hepatic failure including deaths have been reported in patients with serious underlying medical conditions (e.g., hematologic malignancy) during treatment with posaconazole. These severe hepatic reactions were seen primarily in subjects receiving the Noxafil® (posaconazole) oral suspension 800 mg daily (400 mg twice daily or 200 mg four times a day) in clinical trials.

Liver tests should be evaluated at the start of and during the course of posaconazole therapy. Patients who develop abnormal liver tests during posaconazole therapy should be monitored for the development of more severe hepatic injury. Patient management should include laboratory evaluation of hepatic function (particularly liver tests and bilirubin). Discontinuation of posaconazole must be considered if clinical signs and symptoms consistent with liver disease develop that may be attributable to posaconazole.

5.6 Renal Impairment

Posaconazole injection should be avoided in patients with moderate or severe renal impairment (eGFR <50 mL/min), unless an assessment of the benefit/risk to the patient justifies the use of posaconazole injection. In patients with moderate or severe renal impairment (eGFR <50 mL/min), receiving the posaconazole injection, accumulation of the intravenous vehicle, SBECD, is expected to occur. Serum creatinine levels should be closely monitored in these patients, and, if increases occur, consideration should be given to changing to oral posaconazole therapy [see Dosage and Administration (2.9) and Use in Specific Populations (8.6)].

5.7 Midazolam Toxicity

Concomitant administration of posaconazole with midazolam increases the midazolam plasma concentrations by approximately 5-fold. Increased plasma midazolam concentrations could potentiate and prolong hypnotic and sedative effects. Patients must be monitored closely for adverse effects associated with high plasma concentrations of midazolam and benzodiazepine receptor antagonists must be available to reverse these effects [see Drug Interactions (7.5) and Clinical Pharmacology (12.3)].

5.8 Vincristine Toxicity

Concomitant administration of azole antifungals, including posaconazole, with vincristine has been associated with neurotoxicity and other serious adverse reactions, including seizures, peripheral neuropathy, syndrome of inappropriate antidiuretic hormone secretion, and paralytic ileus. Reserve azole antifungals, including Posaconazole, for patients receiving a vinca alkaloid, including vincristine, who have no alternative antifungal treatment options [see Drug Interactions (7.10)].

5.11 Venetoclax Toxicity

Concomitant administration of posaconazole, a strong CYP3A4 inhibitor, with venetoclax may increase venetoclax toxicities, including the risk of tumor lysis syndrome (TLS), neutropenia, and serious infections. In patients with CLL/SLL, administration of posaconazole during initiation and the ramp-up phase of venetoclax is contraindicated [see Contraindications (4.6)]. Refer to the venetoclax labeling for safety monitoring and dose reduction in the steady daily dosing phase in CLL/SLL patients.

For patients with acute myeloid leukemia (AML), dose reduction and safety monitoring are recommended across all dosing phases when coadministering posaconazole with venetoclax [see Drug Interactions (7.16)]. Refer to the venetoclax prescribing information for dosing instructions.

6 ADVERSE REACTIONS

The following serious and otherwise important adverse reactions are discussed in detail in another section of the labeling:
• Hypersensitivity [see Contraindications (4.1)]
• Arrhythmias and QT Prolongation [see Warnings and Precautions (5.2)]
• Hepatic Toxicity [see Warnings and Precautions (5.5)]

6.1 Clinical Trials Experience

Table 16: Posaconazole Pediatric Study: Changes in Liver Tests from CTC Grade 0, 1, or 2 at Baseline to Grade 3 or 4

Number (%) of Patients with Change*
Pediatric Study 1
Laboratory Parameter | Posaconazole Injection and Noxafil® PowderMix (posaconazole) for delayed-release oral suspension (6 mg/kg daily) n=49 (%)
AST | 2/49 (4)
ALT | 3/49 (6)
Bilirubin | 0/48 (0)
Alkaline Phosphatase | 0/48 (0)
*Change from Grade 0 to 2 at baseline to Grade 3 or 4 during the study. These data are presented in the form X/Y, where X represents the number of patients who met the criterion as indicated, and Y represents the number of patients who had a baseline observation and at least one post-baseline observation.
CTC = Common Toxicity Criteria; AST= Aspartate Aminotransferase; ALT= Alanine Aminotransferase

6.2 Postmarketing Experience

The following adverse reaction has been identified during the post-approval use of posaconazole. Because these reactions are reported voluntarily from a population of uncertain size, it is not always possible to reliably estimate their frequency.

Endocrine Disorders: Pseudoaldosteronism

7 DRUG INTERACTIONS

Posaconazole is primarily metabolized via UDP glucuronosyltransferase and is a substrate of p- glycoprotein (P-gp) efflux. Therefore, inhibitors or inducers of these clearance pathways may affect posaconazole plasma concentrations. Coadministration of drugs that can decrease the plasma concentrations of posaconazole should generally be avoided unless the benefit outweighs the risk. If such drugs are necessary, patients should be monitored closely for breakthrough fungal infections.

Posaconazole is also a strong inhibitor of CYP3A4. Therefore, plasma concentrations of drugs predominantly metabolized by CYP3A4 may be increased by posaconazole [see Clinical Pharmacology (12.3)].

The following information was derived from data with Noxafil® (posaconazole) oral suspension or early tablet formulation unless otherwise noted. All drug interactions with Noxafil® (posaconazole) oral suspension, except for those that affect the absorption of posaconazole (via gastric pH and motility), are considered relevant to posaconazole injection as well.

7.1 Immunosuppressants Metabolized by CYP3A4

Sirolimus: Concomitant administration of posaconazole with sirolimus increases the sirolimus blood concentrations by approximately 9-fold and can result in sirolimus toxicity. Therefore, posaconazole is contraindicated with sirolimus [see Contraindications (4.2) and Clinical Pharmacology (12.3)].

Tacrolimus: Posaconazole has been shown to significantly increase the Cmax and AUC of tacrolimus. At initiation of posaconazole treatment, reduce the tacrolimus dose to approximately one-third of the original dose. Frequent monitoring of tacrolimus whole blood trough concentrations should be performed during and at discontinuation of posaconazole treatment and the tacrolimus dose adjusted accordingly [see Warnings and Precautions (5.1) and Clinical Pharmacology (12.3)].

Cyclosporine: Posaconazole has been shown to increase cyclosporine whole blood concentrations in heart transplant patients upon initiation of posaconazole treatment. It is recommended to reduce cyclosporine dose to approximately three-fourths of the original dose upon initiation of posaconazole treatment. Frequent monitoring of cyclosporine whole blood trough concentrations should be performed during and at discontinuation of posaconazole treatment and the cyclosporine dose adjusted accordingly [see Warnings and Precautions (5.1) and Clinical Pharmacology (12.3)].

7.2 CYP3A4 Substrates

Concomitant administration of posaconazole with CYP3A4 substrates such as pimozide and quinidine may result in increased plasma concentrations of these drugs, leading to QTc prolongation and cases of torsades de pointes. Therefore, posaconazole is contraindicated with these drugs [see Contraindications (4.3) and Warnings and Precautions (5.2)].

7.3 HMG-CoA Reductase Inhibitors (Statins) Primarily Metabolized Through CYP3A4

Concomitant administration of posaconazole with simvastatin increases the simvastatin plasma concentrations by approximately 10-fold. Therefore, posaconazole is contraindicated with HMG-CoA reductase inhibitors primarily metabolized through CYP3A4 [see Contraindications (4.4) and Clinical Pharmacology (12.3)].

7.4 Ergot Alkaloids

Most of the ergot alkaloids are substrates of CYP3A4. Posaconazole may increase the plasma concentrations of ergot alkaloids (ergotamine and dihydroergotamine) which may lead to ergotism. Therefore, posaconazole is contraindicated with ergot alkaloids [see Contraindications (4.5)].

7.5 Benzodiazepines Metabolized by CYP3A4

Concomitant administration of posaconazole with midazolam increases the midazolam plasma concentrations by approximately 5-fold. Increased plasma midazolam concentrations could potentiate and prolong hypnotic and sedative effects. Concomitant use of posaconazole and other benzodiazepines metabolized by CYP3A4 (e.g., alprazolam, triazolam) could result in increased plasma concentrations of these benzodiazepines. Patients must be monitored closely for adverse effects associated with high plasma concentrations of benzodiazepines metabolized by CYP3A4 and benzodiazepine receptor antagonists must be available to reverse these effects [see Warnings and Precautions (5.7) and Clinical Pharmacology (12.3)].

7.6 Anti-HIV Drugs

Efavirenz: Efavirenz induces UDP-glucuronidase and significantly decreases posaconazole plasma concentrations [see Clinical Pharmacology (12.3)]. It is recommended to avoid concomitant use of efavirenz with posaconazole unless the benefit outweighs the risks.

Ritonavir and Atazanavir: Ritonavir and atazanavir are metabolized by CYP3A4 and posaconazole increases plasma concentrations of these drugs [see Clinical Pharmacology (12.3)]. Frequent monitoring of adverse effects and toxicity of ritonavir and atazanavir should be performed during coadministration with posaconazole.

Fosamprenavir: Combining fosamprenavir with posaconazole may lead to decreased posaconazole plasma concentrations. If concomitant administration is required, close monitoring for breakthrough fungal infections is recommended [see Clinical Pharmacology (12.3)].

7.7 Rifabutin

Rifabutin induces UDP-glucuronidase and decreases posaconazole plasma concentrations. Rifabutin is also metabolized by CYP3A4. Therefore, coadministration of rifabutin with posaconazole increases rifabutin plasma concentrations [see Clinical Pharmacology (12.3)]. Concomitant use of posaconazole and rifabutin should be avoided unless the benefit to the patient outweighs the risk. However, if concomitant administration is required, close monitoring for breakthrough fungal infections as well as frequent monitoring of full blood counts and adverse reactions due to increased rifabutin plasma concentrations (e.g., uveitis, leukopenia) are recommended.

7.8 Phenytoin

Phenytoin induces UDP-glucuronidase and decreases posaconazole plasma concentrations. Phenytoin is also metabolized by CYP3A4. Therefore, coadministration of phenytoin with posaconazole increases phenytoin plasma concentrations [see Clinical Pharmacology (12.3)]. Concomitant use of posaconazole and phenytoin should be avoided unless the benefit to the patient outweighs the risk. However, if concomitant administration is required, close monitoring for breakthrough fungal infections is recommended and frequent monitoring of phenytoin concentrations should be performed while coadministered with posaconazole and dose reduction of phenytoin should be considered.

7.10 Vinca Alkaloids

Most of the vinca alkaloids (e.g., vincristine and vinblastine) are substrates of CYP3A4. Concomitant administration of azole antifungals, including posaconazole, with vincristine has been associated with serious adverse reactions [see Warnings and Precautions (5.8)]. Posaconazole may increase the plasma concentrations of vinca alkaloids which may lead to neurotoxicity and other serious adverse reactions. Therefore, reserve azole antifungals, including posaconazole, for patients receiving a vinca alkaloid, including vincristine, who have no alternative antifungal treatment options.

7.11 Calcium Channel Blockers Metabolized by CYP3A4

Posaconazole may increase the plasma concentrations of calcium channel blockers metabolized by CYP3A4 (e.g., verapamil, diltiazem, nifedipine, nicardipine, felodipine). Frequent monitoring for adverse reactions and toxicity related to calcium channel blockers is recommended during coadministration. Dose reduction of calcium channel blockers may be needed.

7.12 Digoxin

Increased plasma concentrations of digoxin have been reported in patients receiving digoxin and posaconazole. Therefore, monitoring of digoxin plasma concentrations is recommended during coadministration.

7.14 Glipizide

Although no dosage adjustment of glipizide is required, it is recommended to monitor glucose concentrations when posaconazole and glipizide are concomitantly used.

7.16 Venetoclax

Concomitant use of venetoclax (a CYP3A4 substrate) with posaconazole increases venetoclax Cmax and AUC0-INF, which may increase venetoclax toxicities [see Contraindications (4.6), Warnings and Precautions (5.11)]. Refer to the venetoclax prescribing information for more information on the dosing instructions and the extent of increase in venetoclax exposure.

8 USE IN SPECIFIC POPULATIONS

8.1 Pregnancy

Risk Summary

Based on findings from animal data, posaconazole may cause fetal harm when administered to pregnant women. Available data for use of posaconazole in pregnant women are insufficient to establish a drug-associated risk of major birth defects, miscarriage, or adverse maternal or fetal outcomes. In animal reproduction studies, skeletal malformations (cranial malformations and missing ribs) and maternal toxicity (reduced food consumption and reduced body weight gain) were observed when posaconazole was dosed orally to pregnant rats during organogenesis at doses ≥1.4 times the 400 mg twice daily oral suspension regimen based on steady-state plasma concentrations of posaconazole in healthy volunteers. In pregnant rabbits dosed orally during organogenesis, increased resorptions, reduced litter size, and reduced body weight gain of females were seen at doses 5 times the exposure achieved with the 400 mg twice daily oral suspension regimen. Doses of ≥ 3 times the clinical exposure caused an increase in resorptions in these rabbits (see Data). Based on animal data, advise pregnant women of the potential risk to a fetus.

The estimated background risk of major birth defects and miscarriage for the indicated population is unknown. All pregnancies have a background risk of birth defect, loss, or other adverse outcomes. In the U.S. general population, the estimated background risk of major birth defects and miscarriage in clinically recognized pregnancies is 2 to 4% and 15 to 20%, respectively.

Data

Animal Data

Posaconazole resulted in maternal toxicity (reduced food consumption and reduced body weight gain) and skeletal malformations (cranial malformations and missing ribs) when given orally to pregnant rats during organogenesis (Gestational Days 6 through 15) at doses ≥27 mg/kg (≥1.4 times the 400 mg twice daily oral suspension regimen based on steady-state plasma concentrations of drug in healthy volunteers). The no-effect dose for malformations and maternal toxicity in rats was 9 mg/kg, which is 0.7 times the exposure achieved with the 400 mg twice daily oral suspension regimen. No malformations were seen in rabbits dosed during organogenesis (Gestational Days 7 through 19) at doses up to 80 mg/kg (5 times the exposure achieved with the 400 mg twice daily oral suspension regimen). In the rabbit, the no-effect dose was 20 mg/kg, while high doses of 40 mg/kg and 80 mg/kg (3 or 5 times the clinical exposure) caused an increase in resorptions. In rabbits dosed at 80 mg/kg, a reduction in body weight gain of females and a reduction in litter size were seen.

8.2 Lactation

Risk Summary

There are no data on the presence of posaconazole in human milk, the effects on the breastfed infant, or the effects on milk production. Posaconazole is excreted in the milk of lactating rats. When a drug is present in animal milk, it is likely that the drug will be present in human milk. The developmental and health benefits of breastfeeding should be considered along with the mother’s clinical need for posaconazole and any potential adverse effects on the breastfed child from posaconazole or from the underlying maternal condition.

8.4 Pediatric Use

The safety and effectiveness of Posaconazole injection for the prophylaxis of invasive Aspergillus and Candida infections have been established in pediatric patients aged 2 and older who are at high risk of developing these infections due to being severely immunocompromised, such as HSCT recipients with GVHD or those with hematologic malignancies with prolonged neutropenia from chemotherapy.

The safety and effectiveness of Posaconazole injection for the treatment of invasive aspergillosis have been established in pediatric patients aged 13 years and older.

Use of posaconazole in these age groups is supported by evidence from adequate and well-controlled studies of posaconazole in adult and pediatric patients and additional pharmacokinetic and safety data in pediatric patients 2 years of age and older [see Adverse Reactions (6.1), Clinical Pharmacology (12.3) and Clinical Studies (14)].

The safety and effectiveness of posaconazole have not been established in pediatric patients younger than 2 years of age.

8.5 Geriatric Use

No overall differences in the safety of Posaconazole injection was observed between geriatric patients and younger adult patients in the clinical trials; therefore, no dosage adjustment is recommended for any formulation of posaconazole in geriatric patients. No clinically meaningful differences in the pharmacokinetics of posaconazole were observed in geriatric patients compared to younger adult patients during clinical trials [see Clinical Pharmacology (12.3)].

Of the 279 patients treated with Posaconazole injection in the Posaconazole Injection Study, 52 (19%) were greater than 65 years of age. Of the 230 patients treated with Noxafil® (posaconazole) delayed-release tablets, 38 (17%) were greater than 65 years of age. Of the 605 patients randomized to Noxafil® (posaconazole) oral suspension in Noxafil Oral Suspension Study 1 and Study 2, 63 (10%) were ≥65 years of age. Of the 288 patients randomized to Posaconazole injection/ Noxafil® (posaconazole) delayed-release tablets in the Aspergillosis Treatment Study, 85 (29%) were ≥65 years of age.

No overall differences in the pharmacokinetics and safety were observed between elderly and young subjects during clinical trials, but greater sensitivity of some older individuals cannot be ruled out.

8.6 Renal Impairment

Posaconazole injection should be avoided in patients with moderate or severe renal impairment (eGFR <50 mL/min), unless an assessment of the benefit/risk to the patient justifies the use of posaconazole injection. In patients with moderate or severe renal impairment (eGFR <50 mL/min), receiving the posaconazole injection, accumulation of the intravenous vehicle, SBECD, is expected to occur. Serum creatinine levels should be closely monitored in these patients, and, if increases occur, consideration should be given to changing to oral posaconazole therapy [see Dosage and Administration (2.9) and Warnings and Precautions (5.6)].

8.7 Hepatic Impairment

After a single oral dose of Noxafil® Oral Suspension 400 mg, the mean AUC was 43%, 27%, and 21% higher in subjects with mild (Child-Pugh Class A, N=6), moderate (Child-Pugh Class B, N=6), or severe (Child-Pugh Class C, N=6) hepatic impairment, respectively, compared to subjects with normal hepatic function (N=18). Compared to subjects with normal hepatic function, the mean Cmax was 1% higher, 40 % higher, and 34% lower in subjects with mild, moderate, or severe hepatic impairment, respectively. The mean apparent oral clearance (CL/F) was reduced by 18%, 36%, and 28% in subjects with mild, moderate, or severe hepatic impairment, respectively, compared to subjects with normal hepatic function. The elimination half-life (t½) was 27 hours, 39 hours, 27 hours, and 43 hours in subjects with normal hepatic function and mild, moderate, or severe hepatic impairment, respectively.

It is recommended that no dose adjustment of posaconazole injection is needed in patients with mild to severe hepatic impairment (Child-Pugh Class A, B, or C) [see Dosage and Administration (2) and Warnings and Precautions (5.5)]. However, a specific study has not been conducted with posaconazole injection.

8.8 Gender

The pharmacokinetics of posaconazole are comparable in males and females. No adjustment in the dosage of posaconazole injection is necessary based on gender.

8.9 Race

The pharmacokinetic profile of posaconazole is not significantly affected by race. No adjustment in the dosage of posaconazole injection is necessary based on race.

8.10 Weight

Pharmacokinetic modeling suggests that patients weighing greater than 120 kg may have lower posaconazole plasma drug exposure. It is, therefore, suggested to closely monitor for breakthrough fungal infections [see Clinical Pharmacology (12.3)].

10 OVERDOSAGE

There is no experience with overdosage of posaconazole injection.

During the clinical trails, some patients received Noxafil® Oral Suspension up to 1600 mg/day with no adverse reactions noted that were different from the lower doses. In addition, accidental overdose was noted in one patient who took 1200 mg twice daily Noxafil® Oral Suspension for 3 days. No related adverse reactions were noted by the investigator.

Posaconazole is not removed by hemodialysis.

11 DESCRIPTION

Posaconazole is an azole antifungal agent. Posaconazole is available as an injection solution to be diluted before intravenous administration.

Posaconazole is designated chemically as 4-[4-[4-[4-[[ (3R,5R)-5-(2,4-difluorophenyl)tetrahydro-5-(1H-1,2,4-triazol-1-ylmethyl)-3-furanyl]methoxy]phenyl]-1-piperazinyl]phenyl]-2-[(1S,2S)-1-ethyl-2-hydroxypropyl]-2,4-dihydro-3H-1,2,4-triazol-3-one with an empirical formula of C37H42F2N8O4 and a molecular weight of 700.8.

The chemical structure is:

Posaconazole is a white powder with a low aqueous solubility.

Posaconazole Injection

Posaconazole injection is available as a clear colorless to yellow, sterile liquid essentially free of foreign matter. Each vial contains 300 mg of posaconazole and the following inactive ingredients: 6.68 g Betadex Sulfobutyl Ether Sodium (SBECD), 0.0033 g edetate disodium dihydrate, hydrochloric acid and sodium hydroxide to adjust the pH to 2.6, and water for injection.

12 CLINICAL PHARMACOLOGY

12.1 Mechanism of Action

Posaconazole is an azole antifungal agent [see Clinical Pharmacology (12.4)].

12.2 Pharmacodynamics

Exposure Response Relationship Prophylaxis: In clinical studies of neutropenic patients who were receiving cytotoxic chemotherapy for acute myelogenous leukemia (AML) or myelodysplastic syndromes (MDS) or hematopoietic stem cell transplant (HSCT) recipients with Graft versus Host Disease (GVHD), a wide range of plasma exposures to posaconazole was noted following administration of Noxafil® Oral Suspension. A pharmacokinetic-pharmacodynamic analysis of patient data revealed an apparent association between average posaconazole concentrations (Cavg) and prophylactic efficacy (Table 17). A lower Cavg may be associated with an increased risk of treatment failure, defined as treatment discontinuation, use of empiric systemic antifungal therapy (SAF), or occurrence of breakthrough invasive fungal infections.

Table 17: Noxafil® Oral Suspension Exposure Analysis (Cavg) in Prophylaxis Trials)
 | Prophylaxis in AML/MDS* |  | Prophylaxis in GVHD†
 | Cavg Range (ng/mL) | Treatment Failure‡ (%) | Cavg Range (ng/mL) | Treatment Failure‡ (%)
Quartile 1 | 90-322 | 54.7 | 22-557 | 44.4
Quartile 2 | 322-490 | 37.0 | 557-915 | 20.6
Quartile 3 | 490-734 | 46.8 | 915-1563 | 17.5
Quartile 4 | 734-2200 | 27.8 | 1563-3650 | 17.5
Cavg = the average Posaconazole concentration when measured at steady state
*Neutropenic patients who were receiving cytotoxic chemotherapy for AML or MDS
† HSCT recipients with GVHD
‡ Defined as treatment discontinuation, use of empiric systemic antifungal therapy (SAF), or occurrence of breakthrough invasive fungal infections

Exposure Response Relationship Treatment of Invasive Aspergillosis:

Across a range of posaconazole plasma minimum concentrations (Cmin, range: 244 to 5663 ng/mL) following administration of posaconazole injection and Noxafil® (posaconazole) delayed-release tablets in patients treated for invasive aspergillosis in Aspergillosis Treatment Study, there was no association between posaconazole Cmin and treatment efficacy [see Clinical Pharmacology (12.3) and Clinical Studies (14.1)]. Similarly, across a range of population pharmacokinetic model-predicted steady-state plasma average concentrations (Cavg, range: 589 to 6315 ng/mL), there was no association between posaconazole Cavg and treatment efficacy.

12.3 Pharmacokinetics

General Pharmacokinetic Characteristics

Posaconazole Injection

Posaconazole injection exhibits dose proportional pharmacokinetics after single doses between 200 and 300 mg in healthy volunteers and patients. The mean pharmacokinetic parameters after single doses with posaconazole injection in healthy volunteers and patients are shown in Table 18.

Table 18: Summary of Mean Pharmacokinetic Parameters (%CV) in Healthy Volunteers (30-minute infusion via peripheral venous line) and Patients (90 minute infusion via central venous line) after Dosing with Posaconazole Injection on Day 1

 | Dose (mg) | n | AUC0-∞ (ng·hr/mL) | AUC0-12 (ng·hr/mL) | Cmax (ng/mL) | t1/2 (hr) | CL (L/hr)
Healthy Volunteers | 200 | 9 | 35400 (50) | 8840 (20) | 2250 (29) | 23.6 (23) | 6.5 (32)
Healthy Volunteers | 300 | 9 | 46400 (26) | 13000 (13) | 2840 (30) | 24.6 (20) | 6.9 (27)
Patients | 200 | 30 | N/D | 5570 (32) | 954 (44) | N/D | N/D
Patients | 300 | 22 | N/D | 8240 (26) | 1590 (62) | N/D | N/D
AUC0-∞ = Area under the plasma concentration-time curve from time zero to infinity;
AUC0-12 = Area under the plasma concentration-time curve from time zero to 12 hr after the first dose on Day 1;
Cmax = maximum observed concentration; t½ = terminal phase half-life; CL = total body clearance;
N/D = Not Determined

Table 19 displays the pharmacokinetic parameters of posaconazole in patients following administration of posaconazole injection 300 mg taken once a day for 10 or 14 days following twice daily dosing on Day 1.

Table 19: Arithmetic Mean (%CV) of PK Parameters in Serial PK-Evaluable Patients Following Dosing of Posaconazole Injection (300 mg)*

Day | N | Cmax (ng/mL) | Tmax † (hr) | AUC0-24 (ng*hr/mL) | Cav (ng/mL) | Cmin (ng/mL)
10/14 | 49 | 3280 (74) | 1.5 (0.98-4.0) | 36100 (35) | 1500 (35) | 1090 (44)
AUC0-24 = area under the concentration-time curve over the dosing interval (i.e. 24 hours); Cav= time-averaged concentrations (i.e., AUC0-24h/24hr);
Cmin = POS trough level immediately before a subject received the dose of POS on the day specified in the protocol; Cmax = observed maximum plasma concentration; CV = coefficient of variation, expressed as a percent (%); Day = study day on treatment; Tmax = time of observed maximum plasma concentration.
* 300 mg dose administered over 90 minutes once a day following twice daily dosing on Day 1
† Median (minimum-maximum)

Distribution:

The mean volume of distribution of posaconazole after intravenous solution administration was 261 L and ranged from 226-295 L between studies and dose levels.

Posaconazole is highly bound to human plasma proteins (>98%), predominantly to albumin.

Metabolism:

Posaconazole primarily circulates as the parent compound in plasma. Of the circulating metabolites, the majority are glucuronide conjugates formed via UDP glucuronidation (phase 2 enzymes). Posaconazole does not have any major circulating oxidative (CYP450 mediated) metabolites. The excreted metabolites in urine and feces account for ~17% of the administered radiolabeled dose.

Posaconazole is primarily metabolized via UDP glucuronidation (phase 2 enzymes) and is a substrate for p-glycoprotein (P-gp) efflux. Therefore, inhibitors or inducers of these clearance pathways may affect posaconazole plasma concentrations. A summary of drugs studied clinically with the oral suspension or an early tablet formulation, which affect posaconazole concentrations, is provided in Table 27.

Table 27: Summary of the Effect of Coadministered Drugs on Posaconazole in Healthy Volunteers

Coadministered Drug (Postulated Mechanism of Interaction) | Coadministered Drug Dose/Schedule | Posaconazole Dose/Schedule | Effect on Bioavailability of Posaconazole
Coadministered Drug (Postulated Mechanism of Interaction) | Coadministered Drug Dose/Schedule | Posaconazole Dose/Schedule | Change in Mean C max (ratio estimate*; 90% CI of the ratio estimate) | Change in Mean AUC (ratio estimate*; 90% CI of the ratio estimate)
Efavirenz (UDP-G Induction) | 400 mg once daily × 10 and 20 days | 400 mg (oral suspension) twice daily × 10 and 20 days | ↓45% (0.55; 0.47-0.66) | ↓ 50% (0.50; 0.43-0.60)
Fosamprenavir (unknown mechanism) | 700 mg twice daily x 10 days | 200 mg once daily on the 1st day, 200 mg twice daily on the 2nd day, then 400 mg twice daily x 8 Days | ↓21% 0.79 (0.71-0.89) | ↓23% 0.77 (0.68-0.87)
Rifabutin (UDP-G Induction) | 300 mg once daily x 17 days | 200 mg (tablets) once daily × 10 days† | ↓ 43% (0.57; 0.43-0.75) | ↓ 49% (0.51; 0.37-0.71)
Phenytoin (UDP-G Induction) | 200 mg once daily x 10 days | 200 mg (tablets) once daily × 10 days† | ↓ 41% (0.59; 0.44-0.79) | ↓ 50% (0.50; 0.36-0.71)
*Ratio Estimate is the ratio of coadministered drug plus posaconazole to posaconazole alone for Cmax or AUC.
† The tablet refers to a non-commercial tablet formulation without polymer.

In vitro studies with human hepatic microsomes and clinical studies indicate that posaconazole is an inhibitor primarily of CYP3A4. A clinical study in healthy volunteers also indicates that posaconazole is a strong CYP3A4 inhibitor as evidenced by a >5-fold increase in midazolam AUC. Therefore, plasma concentrations of drugs predominantly metabolized by CYP3A4 may be increased by posaconazole. A summary of the drugs studied clinically, for which plasma concentrations were affected by posaconazole, is provided in Table 28 [see Contraindications (4) and Drug Interactions (7.1) including recommendations].

Table 28: Summary of the Effect of Posaconazole Coadiministered Drugs in Healthy Adult Volunteers and Patients

Coadministered Drug (Postulated Mechanism of Interaction is Inhibition of CYP3A4 by posaconazole) | Coadministered Drug Dose/Schedule | Posaconazole Dose/Schedule | Effect on Bioavailability of Coadministered Drugs
Coadministered Drug (Postulated Mechanism of Interaction is Inhibition of CYP3A4 by posaconazole) | Coadministered Drug Dose/Schedule | Posaconazole Dose/Schedule | Change in Mean C max (ratio estimate*; 90% CI of the ratio estimate) | Change in Mean AUC (ratio estimate*; 90% CI of the ratio estimate)
Sirolimus | 2-mg single oral dose | 400 mg (oral suspension) twice daily × 16 days | ↑572% (6.72; 5.62-8.03) | ↑ 788% (8.88; 7.26-10.9)
Cyclosporine | Stable maintenance dose in heart transplant recipients | 200 mg (tablets) once daily x 10 days† | ↑ cyclosporine whole blood trough concentrations Cyclosporine dose reductions of up to 29% were required
Tacrolimus | 0.05-mg/kg single oral dose | 400 mg (oral suspension) twice daily × 7 days | ↑ 121% (2.21; 2.01-2.42) | ↑ 358% (4.58; 4.03-5.19)
Simvastatin | 40-mg single oral dose | 100 mg (oral suspension) once daily × 13 days 200 mg (oral suspension) once daily x 13 days | Simvastatin ↑ 841% (9.41, 7.13-12.44) Simvastatin Acid ↑ 817% (9.17, 7.36-11.43) Simvastatin ↑1041% (11.41, 7.99-16.29) Simavastatin Acid ↑851% (9.51, 8.15-11.10) | Simvastatin ↑ 931% (10.31, 8.40-12.67) Simvastatin Acid ↑ 634% (7.34, 5.82-9.25) Simvastatin ↑960% (10.60, 8.63-13.02) Simavastatin Acid ↑748% (8.48, 7.04-10.23)
Midazolam | 0.4-mg single intravenous dose‡ 0.4-mg single intravenous dose‡ 2-mg single oral dose‡ 2-mg single oral dose‡ | 200 mg (oral suspension) twice daily x 7 days 400 mg (oral suspension) twice daily x 7 days 200 mg (oral suspension) once daily x 7 days 400 mg (oral suspension) twice daily x 7 days | ↑ 30% (1.3; 1.13-1.48) ↑62% (1.62; 1.41-1.86) ↑ 169% (2.69; 2.46-2.93) ↑ 138% (2.38; 2.13-2.66) | ↑ 362% (4.62; 4.02-5.3) ↑524% (6.24; 5.43-7.16) ↑ 470% (5.70; 4.82-6.74) ↑ 397% (4.97; 4.46-5.54)
Rifabutin | 300 mg once daily x 17 days | 200 mg (tablets) once daily x 10 days† | ↑ 31% (1.31; 1.10-1.57) | ↑ 72% (1.72; 1.51-1.95)
Phenytoin | 200 mg once daily PO x 10 days | 200 mg (tablets) once daily x 10 days† | ↑ 16% (1.16; 0.85-1.57) | ↑ 16% (1.16; 0.84-1.59)
Ritonavir | 100 mg once daily x 14 days | 400 mg (oral suspension) twice daily x 7 days | ↑ 49% (1.49; 1.04-2.15) | ↑ 80% (1.8; 1.39-2.31)
Atazanavir Atazanavir/ritonavir boosted regimen | 300 mg once daily x 14 days 300 mg/100 mg once daily x 14 days | 400 mg (oral suspension) twice daily x 7 days 400 mg (oral suspension) twice daily x 7 days | ↑ 155% (2.55; 1.89-3.45) ↑ 53% (1.53; 1.13-2.07) | ↑ 268% (3.68; 2.89-4.70) ↑ 146% (2.46; 1.93-3.13)
*Ratio Estimate is the ratio of coadministered drug plus posaconazole to coadministered drug alone for Cmax or AUC.
† The tablet refers to a non-commercial tablet formulation without polymer.
‡ The mean terminal half-life of midazolam was increased from 3 hours to 7 to 11 hours during coadministration with posaconazole.

Additional clinical studies demonstrated that no clinically significant effects on zidovudine, lamivudine, indinavir, or caffeine were observed when administered with posaconazole 200 mg once daily; therefore, no dose adjustments are required for these coadministered drugs when coadministered with posaconazole 200 mg once daily.

Excretion:

Following administration of Noxafil® Oral Suspension, posaconazole is predominantly eliminated in the feces (71% of the radiolabeled dose up to 120 hours) with the major component eliminated as parent drug (66% of the radiolabeled dose). Renal clearance is a minor elimination pathway, with 13% of the radiolabeled dose excreted in urine up to 120 hours (<0.2% of the radiolabeled dose is parent drug).

Posaconazole injection is eliminated with a mean terminal half-life (t½) of 27 hours and a total body clearance (CL) of 7.3 L/h.

Specific Populations

No clinically significant differences in the pharmacokinetics of posaconazole were observed based on age, sex, renal impairment, and indication (prophylaxis or treatment).

Race/Ethnicity:

In a population pharmacokinetic analysis of posaconazole, AUC was found to be 25% higher in Chinese patients relative to patients from other races/ethnicities. This higher exposure is not expected to be clinically relevant given the expected variability in posaconazole exposure.

Patients Weighing More Than 120 kg:

Weight has a clinically significant effect on posaconazole clearance. Relative to 70 kg patients, the Cavg is decreased by 25% in patients greater than 120 kg. Patients administered posaconazole weighing more than 120 kg may be at higher risk for lower posaconazole plasma concentrations compared to lower weight patients [see Use in Specific Populations (8.10)].

Pediatric Patients

The mean pharmacokinetic parameters after multiple-dose administration of Posaconazole injection and Noxafil® PowderMix (posaconazole) for delayed-release oral suspension in neutropenic pediatric patients 2 to less than 18 years of age are shown in Table 29. Patients were enrolled into 2 age groups and received Posaconazole injection and Noxafil® PowderMix (posaconazole) for delayed-release oral suspension doses at 6 mg/kg (0.6 to 1 times the recommended dose) with a maximum 300 mg dose once daily (twice daily on Day 1) [see Adverse Reactions (6.1)].

Table 29: Summary of Steady-State Geometric Mean Pharmacokinetic Parameters (% Geometric CV) After Multiple Dosing with Posaconazole Injection and Noxafil® PowderMix (posaconazole) for delayed-release oral suspension 6 mg/kg* in Pediatric Patients with Neutropenia or Expected Neutropenia

Age Group | Dose Type | N | AUC0-24hr (ng·hr/mL) | Cav† (ng/mL) | Cmax (ng/mL) | Cmin (ng/mL) | Tmax‡ (hr) | CL/F§ (L/hr)
2 to <7 years | IV | 17 | 31100 (48.9) | 1300 (48.9) | 3060 (54.1) | 626 (104.8) | 1.75 (1.57-1.83) | 3.27 (49.3)
2 to <7 years | PFS | 7 | 23000 (47.3) | 960 (47.3) | 1510 (43.4) | 542 (68.8) | 4.00 (2.17-7.92) | 4.60 (35.2)
7 to 17 years | IV | 24 | 44200 (41.5) | 1840 (41.5) | 3340 (39.4) | 1160 (60.4) | 1.77 (1.33-6.00) | 4.76 (55.7)
7 to 17 years | PFS | 12 | 25000 (184.3) | 1040 (184.3) | 1370 (178.5) | 713 (300.6) | 2.78 (0.00-4.00) | 8.39 (190.3)
IV= Posaconazole injection; PFS= Noxafil® PowderMix (posaconazole) for delayed-release oral suspension; AUC0-24 = Area under the plasma concentration-time curve from time zero to 24 hr; Cmax = maximum observed concentration; Cmin = minimum observed plasma concentration; Tmax = time of maximum observed concentration; CL /F = apparent total body clearance
*0.6 to 1 times the recommended dose
†Cav = time-averaged concentrations (i.e., AUC0-24hr/24hr)
‡Median (minimum-maximum)
§Clearance (CL for IV and CL/F for PFS)

Based on a population pharmacokinetic model evaluating posaconazole pharmacokinetics and predicting exposures in pediatric patients, the exposure of steady-state posaconazole average concentration greater than or equal to 700 ng/mL in approximately 90% of patients is attained with the recommended dose of Posaconazole injection and Noxafil® PowderMix (posaconazole) for delayed-release oral suspension.

The population pharmacokinetic analysis of posaconazole in pediatric patients suggests that age, sex, renal impairment and ethnicity have no clinically meaningful effect on the pharmacokinetics of posaconazole.

12.4 Microbiology

Mechanism of Action:

Posaconazole blocks the synthesis of ergosterol, a key component of the fungal cell membrane, through the inhibition of cytochrome P-450 dependent enzyme lanosterol 14α-demethylase responsible for the conversion of lanosterol to ergosterol in the fungal cell membrane. This results in an accumulation of methylated sterol precursors and a depletion of ergosterol within the cell membrane thus weakening the structure and function of the fungal cell membrane. This may be responsible for the antifungal activity of posaconazole.

Resistance:

Clinical isolates of Candida albicans and Candida glabrata with decreased susceptibility to posaconazole were observed in oral swish samples taken during prophylaxis with posaconazole and fluconazole, suggesting a potential for development of resistance. These isolates also showed reduced susceptibility to other azoles, suggesting cross-resistance between azoles. The clinical significance of this finding is not known.

Antimicrobial Activity:

Posaconazole has been shown to be active against most isolates of the following microorganisms, both in vitro and in clinical infections [see Indications and Usage (1)].

Microorganisms:

Aspergillus spp. and Candida spp.

Susceptibility Testing:

For specific information regarding susceptibility test interpretive criteria and associated test methods and quality control standards recognized by FDA for this drug, please see: https://www.fda.gov/STIC.

13 NONCLINICAL TOXICOLOGY

13.1 Carcinogenesis, Mutagenesis, Impairment of Fertility

Carcinogenesis

No drug-related neoplasms were recorded in rats or mice treated with posaconazole for 2 years at doses higher than the clinical dose. In a 2-year carcinogenicity study, rats were given posaconazole orally at doses up to 20 mg/kg (females), or 30 mg/kg (males). These doses are equivalent to 3.9- or 3.5-times the exposure achieved with a 400-mg twice daily oral suspension regimen, respectively, based on steady-state AUC in healthy volunteers administered a high-fat meal (400-mg twice daily oral suspension regimen). In the mouse study, mice were treated at oral doses up to 60 mg/kg/day or 4.8-times the exposure achieved with a 400-mg twice daily oral suspension regimen.

Mutagenesis

Posaconazole was not genotoxic or clastogenic when evaluated in bacterial mutagenicity (Ames), a chromosome aberration study in human peripheral blood lymphocytes, a Chinese hamster ovary cell mutagenicity study, and a mouse bone marrow micronucleus study.

Impairment of Fertility

Posaconazole had no effect on fertility of male rats at a dose up to 180 mg/kg (1.7 x the 400-mg twice daily oral suspension regimen based on steady-state plasma concentrations in healthy volunteers) or female rats at a dose up to 45 mg/kg (2.2 x the 400-mg twice daily oral suspension regimen).

13.2 Animal Toxicology and/or Pharmacology

In a nonclinical study using intravenous administration of posaconazole in very young dogs (dosed from 2 to 8 weeks of age), an increase in the incidence of brain ventricle enlargement was observed in treated animals as compared with concurrent control animals. No difference in the incidence of brain ventricle enlargement between control and treated animals was observed following the subsequent 5-month treatment-free period. There were no neurologic, behavioral or developmental abnormalities in the dogs with this finding, and a similar brain finding was not seen with oral posaconazole administration to juvenile dogs (4 days to 9 months of age). There were no drug-related increases in the incidence of brain ventricle enlargement when treated and control animals were compared in a separate study of 10-week old dogs dosed with intravenous posaconazole for 13 weeks with a 9-week recovery period or a follow-up study of 31-week old dogs dosed for 3 months.

14 CLINICAL STUDIES

14.1 Treatment of Invasive Aspergillosis with Posaconazole Injection and Noxafil® (posaconazole) delayed-release tablets

Aspergillosis Treatment Study (NCT01782131) was a randomized, double-blind, controlled trial which evaluated the safety and efficacy of posaconazole injection and Noxafil® (posaconazole) delayed-release tablets versus voriconazole for primary treatment of invasive fungal disease caused by Aspergillus species. Eligible patients had proven, probable, or possible invasive fungal infections per the European Organization for Research and Treatment of Cancer/Mycoses Study Group, EORTC/MSG criteria. Patients were stratified by risk for mortality or poor outcome where high risk included a history of allogeneic bone marrow transplant, liver transplant, or relapsed leukemia undergoing salvage chemotherapy. The median age of patients was 57 years (range 14-91 years), with 27.8% of patients aged ≥65 years; 5 patients were pediatric patients 14- 16 years of age, of whom 3 were treated with posaconazole and 2 with voriconazole. The majority of patients were male (59.8%) and white (67.1%). With regard to risk factors for invasive aspergillosis, approximately two- thirds of the patients in the study had a recent history of neutropenia, while approximately 20% with a history of an allogeneic stem cell transplant. Over 80% of subjects in each treatment group had infection limited to the lower respiratory tract (primarily lung), while approximately 11% to 13% also had infection in another organ. Invasive aspergillosis was proven or probable in 58.1% of patients as classified by independent adjudicators blinded to study treatment assignment. At least one Aspergillus species was identified in 21% of the patients; A. fumigatus and A. flavus were the most common pathogens identified.

Patients randomized to receive posaconazole were given a dose of 300 mg once daily (twice daily on Day 1) IV or tablet. Patients randomized to receive voriconazole were given a dose of 6 mg/kg twice daily Day 1 followed by 4 mg/kg twice daily IV, or oral 300 mg twice daily Day 1 followed by 200 mg twice daily. The recommended initial route of administration was IV; however, patients could begin oral therapy if clinically stable and able to tolerate oral dosing. The transition from IV to oral therapy occurred when the patient was clinically stable. The protocol recommended duration of therapy was 84 days with a maximum allowed duration of 98 days. Median treatment duration was 67 days for posaconazole patients and 64 days for voriconazole patients. Overall, 55% to 60% of patients began treatment with the IV formulation with a median duration of 9 days for the initial IV dosing.

The Intent to Treat (ITT) population included all patients randomized and receiving at least one dose of study treatment. All-cause mortality through Day 42 in the overall population (ITT) was 15.3% for posaconazole patients compared to 20.6% for voriconazole patients for an adjusted treatment difference of -5.3% with a 95% confidence interval of -11.6 to 1.0%. Consistent results were seen in patients with proven or probable invasive aspergillosis per EORTC criteria (see Table 30).

Table 30: Posaconazole Injection and Noxafil® (posaconazole) delayed-release tablets Invasive Aspergillosis Treatment Study: All-Cause Mortality Through Day 42

 | Posaconazole Injection and Delayed-Release Tablets |  | Voriconazole
Population | N | n (%) | N | n (%) | Difference* (95% CI)
Intent to Treat | 288 | 44 (15.3) | 287 | 59 (20.6) | -5.3 (-11.6, 1.0)
Proven/Probable Invasive Aspergillosis | 163 | 31 (19.0) | 171 | 32 (18.7) | 0.3 (-8.2, 8.8)
*Adjusted treatment difference based on Miettinen and Nurminen’s method stratified by randomization factor (risk for mortality/poor outcome), using Cochran-Mantel-Haenszel weighting scheme.

Global clinical response at Week 6 was assessed by a blinded, independent adjudication committee based upon prespecified clinical, radiologic, and mycologic criteria. In the subgroup of patients with proven or probable invasive aspergillosis per EORTC criteria, the global clinical response of success (complete or partial response) at Week 6 was seen in 44.8% for posaconazole-treated patients compared to 45.6% for voriconazole-treated patients (see Table 31).

Table 31: Posaconazole Injection and Noxafil® (posaconazole) delayed-release tablets Invasive Aspergillosis Treatment Study: Successful Global Clinical Response* at Week 6

 | Posaconazole |  | Voriconazole
Population | N | Success | N | Success | Difference† (95% CI)
Proven/Probable Invasive Aspergillosis | 163 | 73 (44.8) | 171 | 78 (45.6) | -0.6 (-11.2, 10.1)
*Successful Global Clinical Response was defined as survival with a partial or complete response.
†Adjusted treatment difference based on Miettinen and Nurminen’s method stratified by randomization factor (risk for mortality/poor outcome), using Cochran-Mantel-Haenszel weighting scheme.

14.2 Prophylaxis of Aspergillus and Candida Infections with Noxafil® Oral Suspension

Two randomized, controlled studies were conducted using posaconazole as prophylaxis for the prevention of invasive fungal infections (IFIs) among patients at high risk due to severely compromised immune systems.

The first study (Noxafil® Oral Suspension Study 1) was a randomized, double-blind trial that compared Noxafil® Oral Suspension (200 mg three times a day) with fluconazole capsules (400 mg once daily) as prophylaxis against invasive fungal infections in allogeneic hematopoietic stem cell transplant (HSCT) recipients with Graft versus Host Disease (GVHD). Efficacy of prophylaxis was evaluated using a composite endpoint of proven/probable IFIs, death, or treatment with systemic antifungal therapy (patients may have met more than one of these criteria). This assessed all patients while on study therapy plus 7 days and at 16 weeks post-randomization. The mean duration of therapy was comparable between the 2 treatment groups (80 days, Noxafil® Oral Suspension; 77 days, fluconazole). Table 32 contains the results from Noxafil® Oral Suspension Study 1.

Table 32: Results from Blinded Clinical Study in Prophylaxis of IFI in All Randomized Patients with Hematopoietic Stem Cell Transplant (HSCT) and Graft-vs.-Host Disease (GVHD): Noxafil® Oral Suspension Study 1
 | Posaconazole n=301 | Fluconazole n=299
On therapy plus 7 days
Clinical Failure* | 50 (17%) | 55 (18%)
Failure due to:
Proven/Probable IFI | 7 (2%) | 22 (7%)
(Aspergillus) | 3 (1%) | 17 (6%)
(Candida) | 1 (<1%) | 3 (1%)
(Other) | 3 (1%) | 2 (1%)
All Deaths | 22 (7%) | 24 (8%)
Proven/probable fungal infection prior to death | 2 (<1%) | 6 (2%)
SAF † | 27 (9%) | 25 (8%)
Through 16 weeks
Clinical Failure*, ‡ | 99 (33%) | 110 (37%)
Failure due to:
Proven/Probable IFI | 16 (5%) | 27 (9%)
(Aspergillus) | 7 (2%) | 21 (7%)
(Candida) | 4 (1%) | 4 (1%)
(Other) | 5 (2%) | 2 (1%)
All Deaths | 58 (19%) | 59 (20%)
Proven/probable fungal infection prior to death | 10 (3%) | 16 (5%)
SAF † | 26 (9%) | 30 (10%)
Event free lost to follow-up§ | 24 (8%) | 30 (10%)

*Patients may have met more than one criterion defining failure.

†Use of systemic antifungal therapy (SAF) criterion is based on protocol definitions (empiric/IFI usage >4 consecutive days).

‡95% confidence interval (posaconazole-fluconazole) = (-11.5%, +3.7%).

§Patients who are lost to follow-up (not observed for 112 days), and who did not meet another clinical failure endpoint. These patients were considered failures.

The second study (Noxafil® Oral Suspension Study 2) was a randomized, open-label study that compared Noxafil® Oral Suspension (200 mg 3 times a day) with fluconazole suspension (400 mg once daily) or itraconazole oral solution (200 mg twice a day) as prophylaxis against IFIs in neutropenic patients who were receiving cytotoxic chemotherapy for AML or MDS. As in Noxafil® Oral Suspension Study 1, efficacy of prophylaxis was evaluated using a composite endpoint of proven/probable IFIs, death, or treatment with systemic antifungal therapy (Patients might have met more than one of these criteria). This study assessed patients while on treatment plus 7 days and 100 days postrandomization. The mean duration of therapy was comparable between the 2 treatment groups (29 days, posaconazole; 25 days, fluconazole or itraconazole). Table 33 contains the results from Noxafil® Oral Suspension Study 2.

Table 33: Results from Open-Label Clinical Study 2 in Prophylaxis of IFI in All Randomized Patients with Hematologic Malignancy and Prolonged Neutropenia: Noxafil® Oral Suspension Study 2
 | Posaconazole n=304 | Fluconazole/Itraconazole n=298
On therapy plus 7 days
Clinical Failure*,† | 82 (27%) | 126 (42%)
Failure due to:
Proven/Probable IFI | 7 (2%) | 25 (8%)
(Aspergillus) | 2 (1%) | 20 (7%)
(Candida) | 3 (1%) | 2 (1%)
(Other) | 2 (1%) | 3 (1%)
All Deaths | 17 (6%) | 25 (8%)
Proven/probable fungal infection prior to death | 1 (<1%) | 2 (1%)
SAF ‡ | 67 (22%) | 98 (33%)
Through 100 days postrandomization
Clinical Failure† | 158 (52%) | 191 (64%)
Failure due to:
Proven/Probable IFI | 14 (5%) | 33 (11%)
(Aspergillus) | 2 (1%) | 26 (9%)
(Candida) | 10 (3%) | 4 (1%)
(Other) | 2 (1%) | 3 (1%)
All Deaths | 44 (14%) | 64 (21%)
Proven/probable fungal infection prior to death | 2 (1%) | 16 (5%)
SAF ‡ | 98 (32%) | 125 (42%)
Event free lost to follow-up§ | 34 (11%) | 24 (8%)

*95% confidence interval (posaconazole-fluconazole/itraconazole) = (-22.9%, -7.8%).

†Patients may have met more than one criterion defining failure.

‡ Use of systemic antifungal therapy (SAF) criterion is based on protocol definitions (empiric/IFI usage >3 consecutive days).

§Patients who are lost to follow-up (not observed for 100 days), and who did not meet another clinical failure endpoint. These patients were considered failures.

In summary, 2 clinical studies of prophylaxis were conducted with the Noxafil® Oral Suspension. As seen in the accompanying tables (Tables 32 and 33), clinical failure represented a composite endpoint of breakthrough IFI, mortality and use of systemic antifungal therapy. In Noxafil® Oral Suspension Study 1 (Table 32), the clinical failure rate of posaconazole (33%) was similar to fluconazole (37%), (95% CI for the difference posaconazole–comparator -11.5% to 3.7%) while in Noxafil® Oral Suspension Study 2 (Table 33) clinical failure was lower for patients treated with posaconazole (27%) when compared to patients treated with fluconazole or itraconazole (42%), (95% CI for the difference posaconazole–comparator -22.9% to -7.8%).

All-cause mortality was similar at 16 weeks for both treatment arms in Noxafil® Oral Suspension Study 1 [POS 58/301 (19%) vs. FLU 59/299 (20%)]; all-cause mortality was lower at 100 days for posaconazole-treated patients in Noxafil® Oral Suspension Study 2 [POS 44/304 (14%) vs. FLU/ITZ 64/298 (21%)]. Both studies demonstrated fewer breakthrough infections caused by Aspergillus species in patients receiving posaconazole prophylaxis when compared to patients receiving fluconazole or itraconazole.

16 HOW SUPPLIED/STORAGE AND HANDLING

16.1 How Supplied

Posaconazole Injection

Posaconazole injection is available as a clear, colorless to yellow sterile liquid in single-dose Type I glass vials closed with bromobutyl rubber stopper and aluminum seal (NDC 68462-911-01) containing 300 mg of posaconazole in 16.7 mL of solution (18 mg of posaconazole per mL).

16.2 Storage and Handling

Posaconazole Injection

Posaconazole injection vial should be stored refrigerated at 2 to 8°C (36 to 46°F). Storage conditions for the diluted solution are presented in another section of the prescribing information [see Dosage and Administration (2.4)].

17 PATIENT COUNSELING INFORMATION

Advise the patient to read the FDA-approved patient labeling (Patient Information).

Important Administration Instructions
Instruct patients that if they miss a dose, they should take it as soon as they remember. However, if it is almost time for the next dose, they should be instructed to skip the missed dose and go back to the regular schedule. Patients should not double their next dose or take more than the prescribed dose.

Drug Interactions
Advise patients to inform their physician immediately if they:
• develop severe diarrhea or vomiting.
• are currently taking drugs that are known to prolong the QTc interval and are metabolized through CYP3A4.
• are currently taking a cyclosporine or tacrolimus, or they notice swelling in an arm or leg or shortness of breath.
• are taking other drugs or before they begin taking other drugs as certain drugs can decrease or increase the plasma concentrations of posaconazole.
Serious and Potentially Serious Adverse Reactions
Advise patients to inform their physician immediately if they:
• notice a change in heart rate or heart rhythm or have a heart condition or circulatory disease. Posaconazole can be administered with caution to patients with potentially proarrhythmic conditions.
• are pregnant, plan to become pregnant, or are nursing.
• have liver disease or develop itching, nausea or vomiting, their eyes or skin turn yellow, they feel more tired than usual or feel like they have the flu.
• have ever had an allergic reaction to other antifungal medicines such as ketoconazole, fluconazole, itraconazole, or voriconazole.

All third party brand names, trademarks and/or trade names are the property of their respective owners.

Distributed by:

Glenmark Pharmaceuticals Inc., USA

Elmwood Park, NJ 07407

Novaplus is a registered trademark of Vizient, Inc.

July 2025

Patient Information

Posaconazole (poe-sa-KONE-a-zole) injection

What is posaconazole injection?

Posaconazole injection is prescription medicine used in adults and children to help prevent or treat fungal infections that can spread throughout your body (invasive fungal infections). These infections are caused by fungi called Aspergillus or Candida. Posaconazole injection is used in people who have an increased chance of getting these infections due to a weak immune system. These include people who have had a hematopoietic stem cell transplantation (bone marrow transplant) with graft versus host disease or those with a low white blood cell count due to chemotherapy for blood cancers (hematologic malignancies).

Posaconazole injection is used for:

- prevention of fungal infections in adults and children 2 years of age and older.
- treatment of fungal infections in adults and children 13 years of age and older.

It is not known if posaconazole injection is safe and effective in children under 2 years of age.

Who should not take posaconazole?

Do not take posaconazole if you:

- are allergic to posaconazole, any of the ingredients in posaconazole injection, or other azole antifungal medicines. See the end of this leaflet for a complete list of ingredients in posaconazole.
- are taking any of the following medicines:
  - sirolimus
  - pimozide
  - quinidine
  - certain statin medicines that lower cholesterol (atorvastatin, lovastatin, simvastatin)
  - ergot alkaloids (ergotamine, dihydroergotamine)
- have chronic lymphocytic leukemia (CLL) or small lymphocytic lymphoma (SLL) and you have just started taking venetoclax or your venetoclax dose is being slowly increased.

Ask your healthcare provider or pharmacist if you are not sure if you are taking any of these medicines.

Do not start taking a new medicine without talking to your healthcare provider or pharmacist.

What should I tell my healthcare provider before taking posaconazole?

Before you take posaconazole, tell your healthcare provider if you:

- are taking certain medicines that lower your immune system like cyclosporine or tacrolimus.
- are taking certain drugs for HIV infection, such as ritonavir, atazanavir, efavirenz, or fosamprenavir. Efavirenz and fosamprenavir can cause a decrease in the posaconazole levels in your body. Efavirenz and fosamprenavir should not be taken with posaconazole.
- are taking midazolam, a hypnotic and sedative medicine.
- are taking vincristine, vinblastine and other “vinca alkaloids” (medicines used to treat cancer).
- are taking venetoclax, a medicine used to treat cancer.
- have or had liver problems.
- have or had kidney problems.
- have or had an abnormal heart rate or rhythm, heart problems, or blood circulation problems.
- are pregnant or plan to become pregnant. It is not known if posaconazole will harm your unborn baby.
- are breastfeeding or plan to breastfeed. It is not known if posaconazole passes into your breast milk. You and your healthcare provider should decide if you will take posaconazole or breastfeed. You should not do both.

Tell your healthcare provider about all the medicines you take, including prescription and over-the-counter medicines, vitamins, and herbal supplements. Posaconazole can affect the way other medicines work, and other medicines can affect the way posaconazole work, and can cause serious side effects.

Ask your healthcare provider or pharmacist for a list of these medicines if you are not sure.

Know the medicines you take. Keep a list of them with you to show your healthcare provider or pharmacist when you get a new medicine.

How will I take posaconazole?

- Take posaconazole exactly as your healthcare provider tells you to take it.
- Your healthcare provider will tell you how much posaconazole to take and when to take it.
- Take posaconazole for as long as your healthcare provider tells you to take it.
- If you take too much posaconazole call your healthcare provider or go to the nearest hospital emergency room right away.
- Posaconazole injection is usually given over 30 to 90 minutes through a plastic tube placed in your vein.

Follow the instructions from your healthcare provider on how much posaconazole injection you should take and when to take it.

What are the possible side effects of posaconazole?

Posaconazole may cause serious side effects, including:

- drug interactions with cyclosporine or tacrolimus. If you take posaconazole with cyclosporine or tacrolimus, your blood levels of cyclosporine or tacrolimus may increase. Serious side effects can happen in your kidney or brain if you have high levels of cyclosporine or tacrolimus in your blood. Your healthcare provider should do blood tests to check your levels of cyclosporine or tacrolimus if you are taking these medicines while taking posaconazole. Tell your healthcare provider right away if you have swelling in your arm or leg or shortness of breath.
- problems with the electrical system of your heart (arrhythmias and QTc prolongation). Certain medicines used to treat fungus called azoles, including posaconazole, the active ingredient in posaconazole, may cause heart rhythm problems. People who have certain heart problems or who take certain medicines have a higher chance for this problem. Tell your healthcare provider right away if your heartbeat becomes fast or irregular.
- changes in body salt (electrolytes) levels in your blood. Your healthcare provider should check your electrolytes while you are taking posaconazole.
- new or worsening high blood pressure and low potassium levels in your blood (pseudoaldosteronism). Your healthcare provider should check your blood pressure and potassium levels.
- liver problems. Some people who also have other serious medical problems may have severe liver problems that may lead to death, especially if you take certain doses of posaconazole. Your healthcare provider should do blood tests to check your liver while you are taking posaconazole. Call your healthcare provider right away if you have any of the following symptoms of liver problems:

- itchy skin

- feeling very tired

- nausea or vomiting

- flu-like symptoms

- yellowing of your eyes or skin

- increased amounts of midazolam in your blood. If you take posaconazole with midazolam, posaconazole increases the amount of midazolam in your blood. This can make your sleepiness last longer. Your healthcare provider should check you closely for side effects if you take midazolam with posaconazole.

The most common side effects of posaconazole in adults include:

- diarrhea

- headache

- nausea

- coughing

- fever

- low potassium levels in the blood

- vomiting

The most common side effects of posaconazole injection in children include:

- fever

- itching

- fever with low white blood cell count (febrile neutropenia)

- high blood pressure

- vomiting

- low potassium levels in the blood

- redness and sores of the lining of the mouth, lips, throat, stomach, and genitals (mucositis or stomatitis)

Tell your healthcare provider if you have any side effect that bothers you or that does not go away.

These are not all the possible side effects of posaconazole. For more information, ask your healthcare provider or pharmacist.

Call your doctor for medical advice about side effects. You may report side effects to FDA at 1-800-FDA-1088.

How should I store posaconazole?

Posaconazole injection

- Store posaconazole injection refrigerated at 36◦F to 46◦F (2◦C to 8◦C).

Safely throw away medicine that is out of date or no longer needed.

Keep posaconazole and all medicines out of the reach of children.

General information about the safe and effective use of posaconazole.

Medicines are sometimes prescribed for purposes other than those listed in a Patient Information leaflet. Do not use posaconazole for a condition for which it was not prescribed. Do not give posaconazole to other people, even if they have the same symptoms that you have. It may harm them. You can ask your pharmacist or healthcare provider for information about posaconazole that is written for health professionals.

What are the ingredients in posaconazole?

Active ingredient: posaconazole

Inactive ingredients:

Posaconazole injection: Betadex Sulfobutyl Ether Sodium (SBECD), edetate sodium dihydrate, hydrochloric acid, sodium hydroxide, and water for injection.

Distributed by:

Glenmark Pharmaceuticals Inc., USA

Elmwood Park, NJ 07407

Novaplus is a registered trademark of Vizient, Inc.

For more information, call 1 (888) 721-7115

This Patient Information has been approved by the U.S. Food and Drug Administration. Revised: July 2025

PACKAGE LABEL.PRINCIPAL DISPLAY PANEL

Carton Label:

NDC 68462-911-01 Rx only

Posaconazole

Injection

300 mg/16.7 mL

(18 mg/mL)

For Intravenous Use Only

Requires further dilution prior to infusion.

Sterile Single-Dose Vial

Discard Unused Portion

Vial Label:

NDC 68462-911-01 Rx only

Posaconazole

Injection

300 mg/16.7 mL

(18 mg/mL)

For Intravenous Use Only

Sterile Single-Dose Vial

Discard Unused Portion